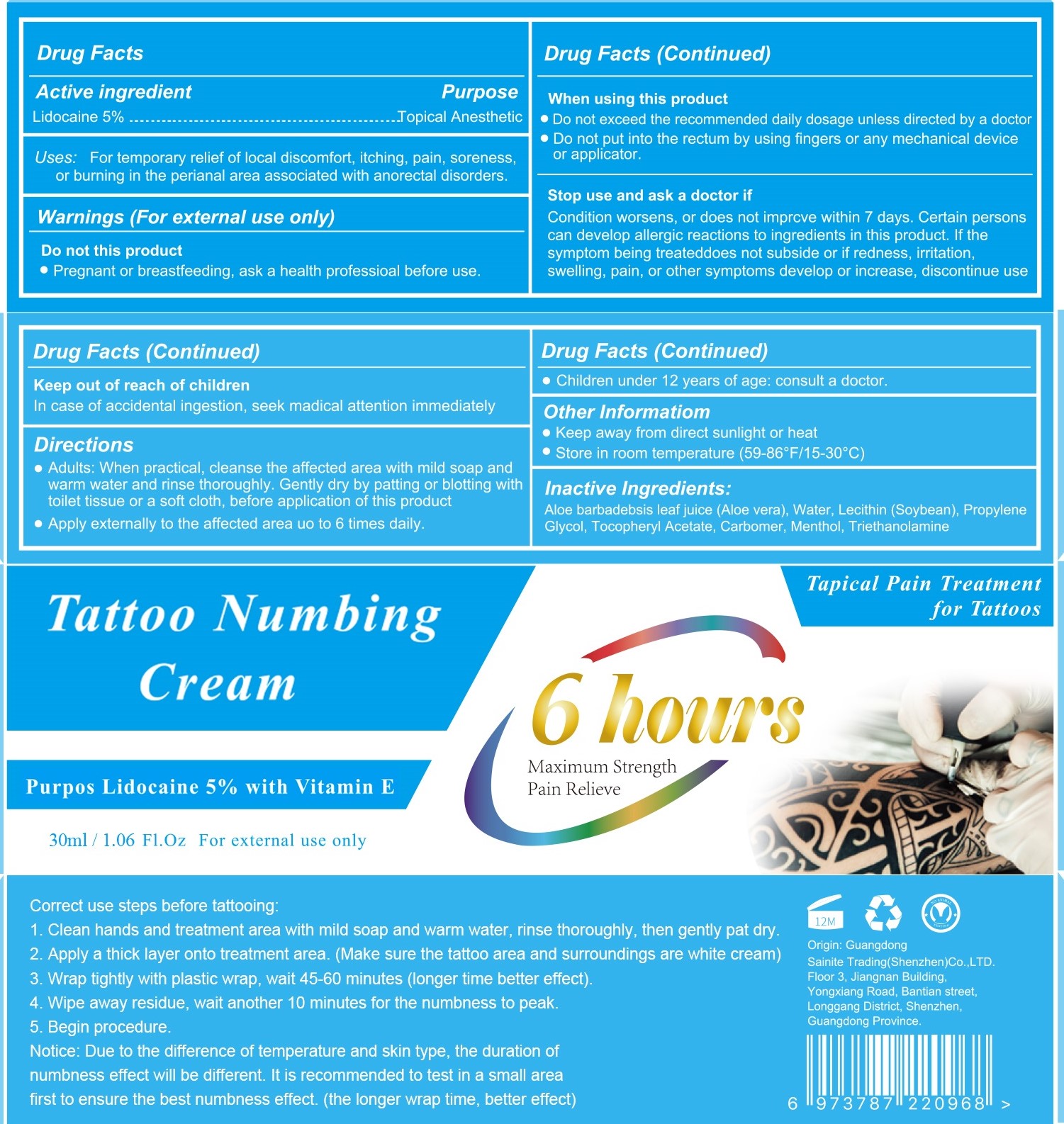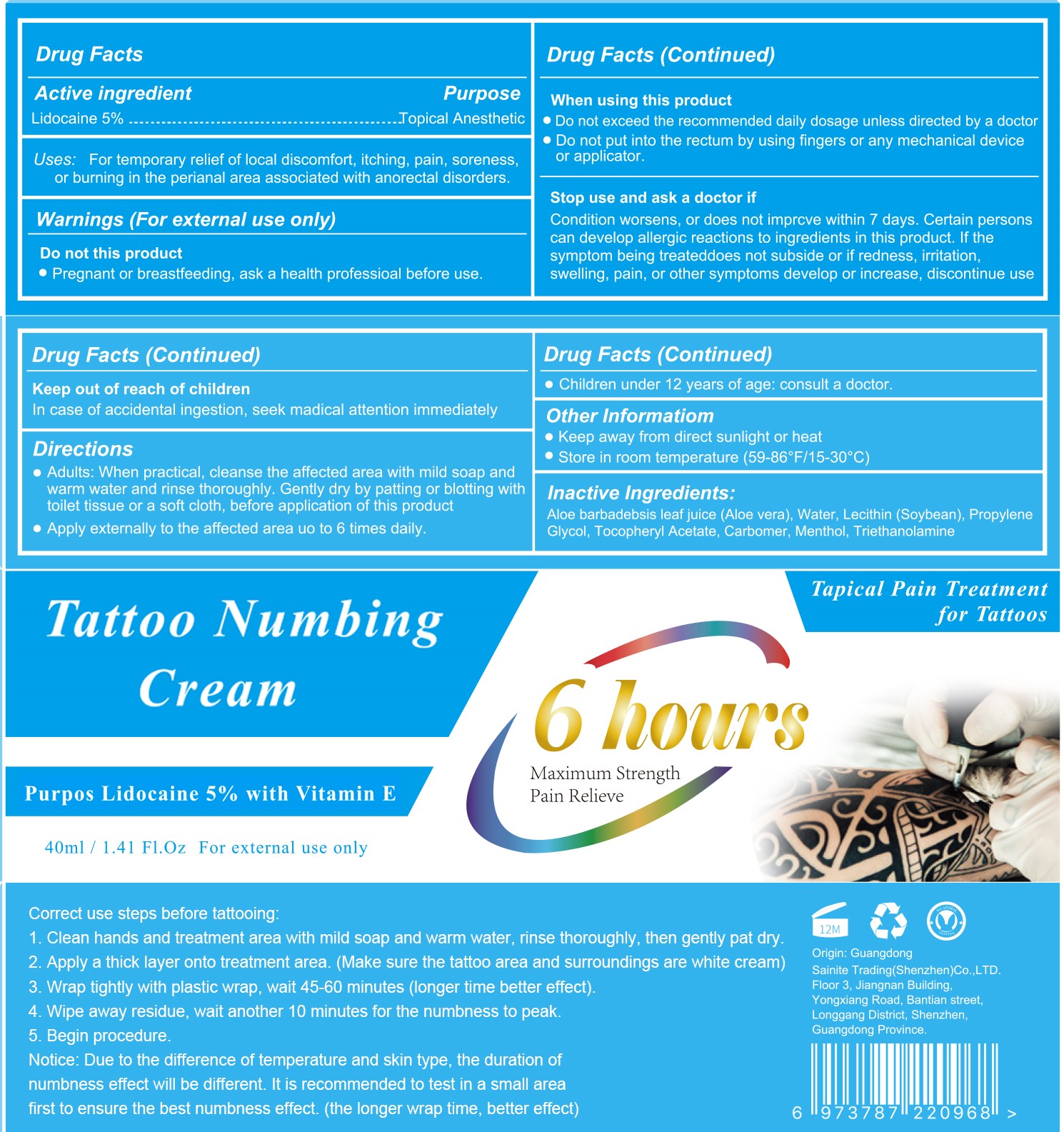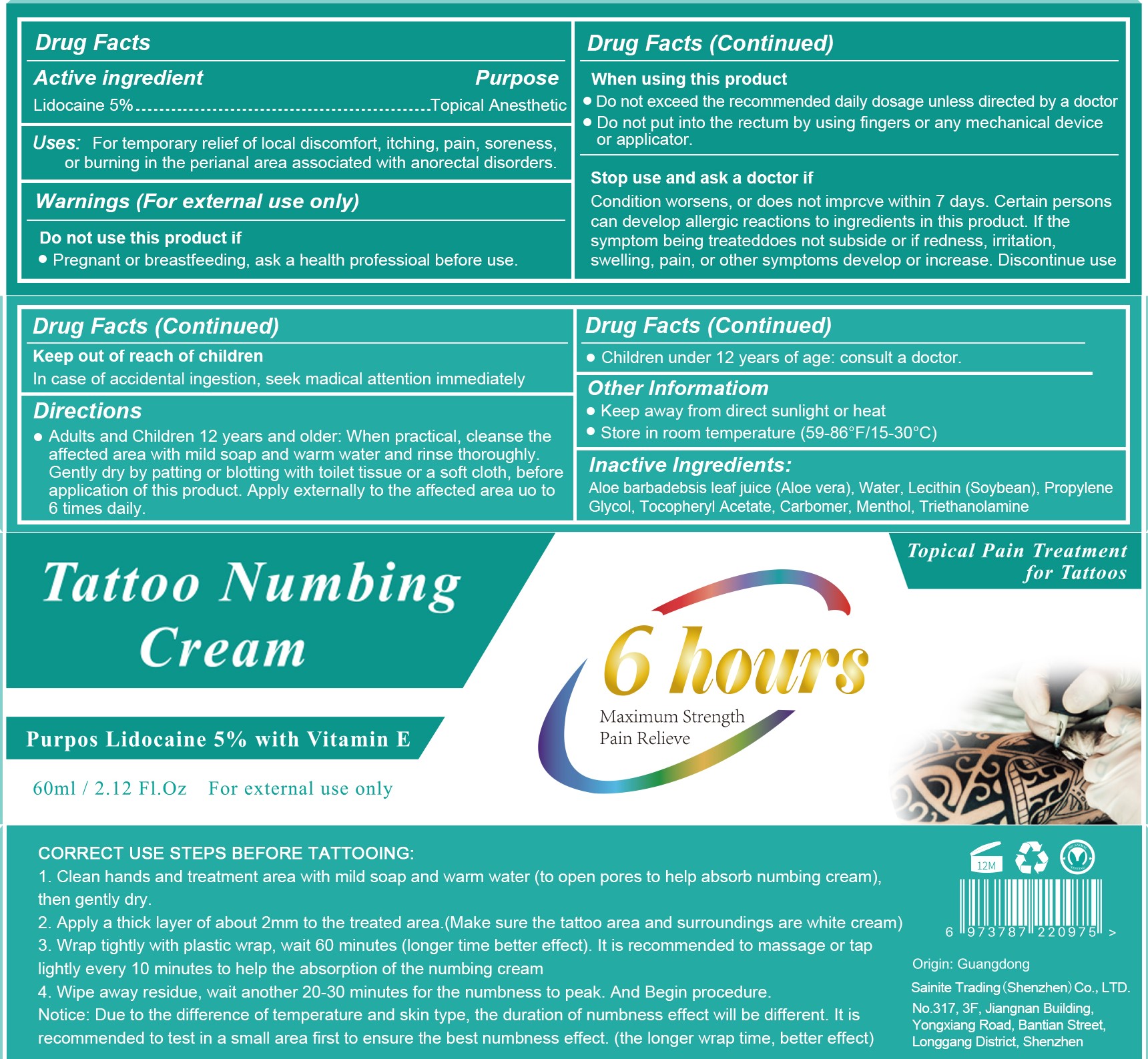 DRUG LABEL: SAMNYTE Tattoo Numbing Cream
NDC: 82929-010 | Form: EMULSION
Manufacturer: Sainite Trading Shenzhen Co., Ltd.
Category: otc | Type: HUMAN OTC DRUG LABEL
Date: 20240123

ACTIVE INGREDIENTS: LIDOCAINE 5 g/100 mL
INACTIVE INGREDIENTS: WATER; CARBOMER HOMOPOLYMER, UNSPECIFIED TYPE; TROLAMINE; ALOE VERA WHOLE; PROPYLENE GLYCOL; MENTHOL; .ALPHA.-TOCOPHEROL ACETATE; LECITHIN, SOYBEAN

82929-010-(01,02,03)

Active Ingredients

Lidocaine 5%

Purpose

Topical Anesthetic

Uses

For temporary relief of local discomfort, itching, pain, soreness, or burning in the perianal area associated with anorectal disorders.

Warnings

For external use only

Do not this product

Pregnant or breastfeeding, ask a health professional before use.

When using this product

Do not exceed the recommended daily dosage unless directed by a doctor
Do not put into the rectum by using fingers or any mechanical device or applicator.

Stop use and ask a doctor if

Condition worsens, or does not imprcve within 7 days. Certain persons can develop allergic reactions to ingredients in this product. If the symptom being treateddoes not subside or if redness, irritation, swelling, pain, or other symptoms develop or increase. Discontinue use

Keep out of reach of children

In case of accidental ingestion, seek madical attention immediately

Directions

Adults and Children 12 years and older: When practical, cleanse the affected area with mild soap and warm water and rinse thotoughly.
Gently dry by patting or blotting with toilet tissue or a soft cloth, before application of this product. Apply externally to the affected area uo to 6 times daily.

Other Informatiom

● Keep away from direct sunlight or heat
● Store in room temperature (59-86°F/15-30°C)

Inactive Ingredients

Aloe barbadebsis leaf juice (Aloe vera), Water, Lecithin (Soybean), Propylene Glycol, Tocopheryl Acetate, Carbomer, Menthol, Triethanolamine